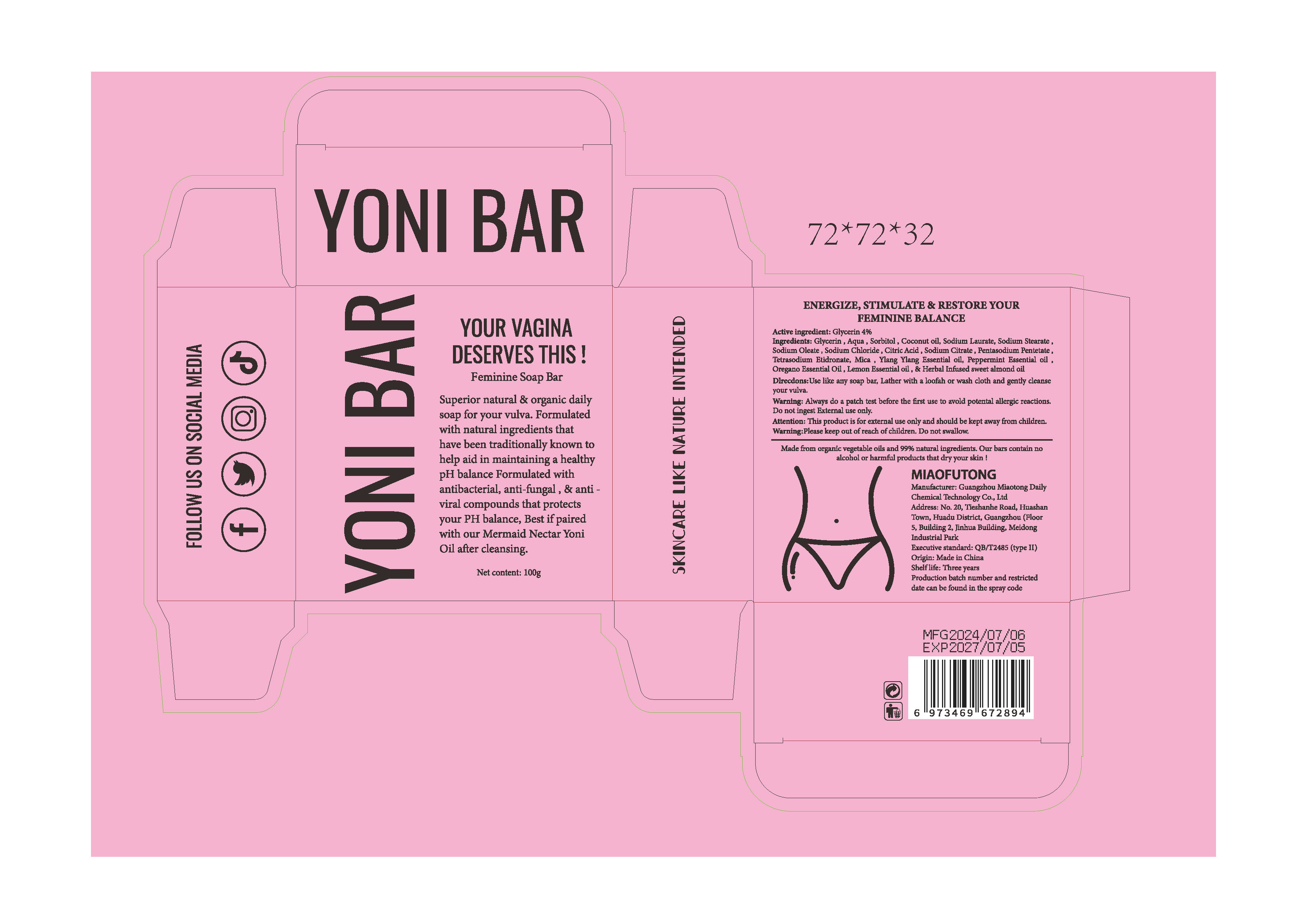 DRUG LABEL: Yoni bar
NDC: 84519-002 | Form: SOAP
Manufacturer: Guangzhou Miaotong Daily Chemical Technology Co., Ltd
Category: otc | Type: HUMAN OTC DRUG LABEL
Date: 20240814

ACTIVE INGREDIENTS: GLYCERIN 4 g/100 g
INACTIVE INGREDIENTS: MICA; WATER; OREGANO LEAF OIL; SODIUM STEARATE; ETIDRONATE TETRASODIUM; ALMOND OIL; COCONUT OIL; SODIUM CHLORIDE; CITRIC ACID MONOHYDRATE; LEMON OIL, TERPENELESS; PENTASODIUM PENTETATE; PEPPERMINT OIL; SODIUM LAURATE; SODIUM CITRATE; SORBITOL; SODIUM OLEATE; YLANG-YLANG OIL

Yoni bar

ACTIVE INGREDIENT

Glycerin 4%

PURPOSE

Feminine Soap Bar

KEEP OUT OF REACH OF CHILDREN SECTION

INDICATIONS AND USAGE

Superior natural & organic dailysoap for your vulva. Formulatedwith natural ingredients thathave been traditionally known tohelp aid in maintaining a healthypH balance Formulated withantibacterial, anti-fungal , & anti -viral compounds that protectsyour PH balance, Best if pairedwith our Mermaid Nectar YoniOil after cleansing.

WARNINGS

Warning:Please keep out of reach of children, Do not swallow.

DOSAGE AND ADMINISTRATION

Dlrecdons:Use like any soap bar, Lather with a loofah or wash cloth and gently cleanseyour vulva.

INACTIVE INGREDIENT

Aqua
Sorbitol
Coconut oil
Sodium Laurate
Sodium Stearate
Sodium Oleate
Sodium Chloride
Citric Acid
Sodium Citrate
Pentasodium Pentetate
Tetrasodium Etidronate
Mica
Ylang Ylang Essential oil
Peppermint Essential oil
Oregano Essential Oil
Lemon Essential oil
& Herbal Infused sweet almond oil